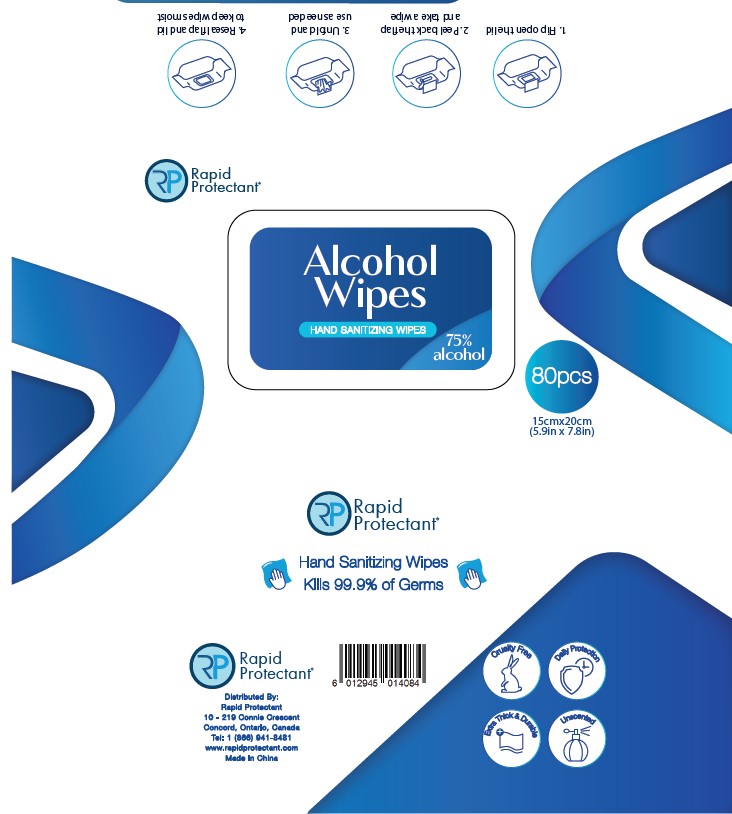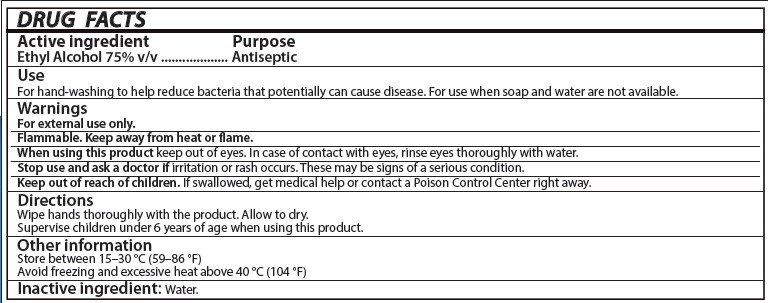 DRUG LABEL: Alcohol wipes Hand Sanitizing Wipes
NDC: 87159-001 | Form: CLOTH
Manufacturer: DGE Essentials Inc
Category: otc | Type: HUMAN OTC DRUG LABEL
Date: 20251014

ACTIVE INGREDIENTS: ALCOHOL 0.75 mL/1 mL
INACTIVE INGREDIENTS: WATER

Alcohol Wipes Hand Sanitizing Wipes

Active Ingredient

Ethyl Alcohol 75% v/v

Purpose

Antiseptic

Uses

For hand-washing to help reduce bacteria that potentially can cause disease. For use when soap and water are not available.

Warnings

For external use only

Flammable. Keep away from heat or flame.

When using this product keep out of eyes. In case of contact with eyes, rinse eyes thoroughly with water.

Stop use and ask a doctor if irritation or rash occurs. These may be signs of a serious condition.

Keep out of reach of children. If swallowed, get medical help or contact a Poison Control Center right away.

Directions

Wipe hands thoroughly with the product. Allow to dry.

Supervise children under 6 years of age when using this product.

Other Information

Store between 15–30 °C (59–86 °F)

Avoid freezing and excessive heat above 40 °C (104 °F)

Inactive Ingredients

Water.

PACKAGE LABEL.PRINCIPAL DISPLAY

Alcohol

Wipes

HAND SANITIZING WIPES

75% Alcohol

Drug Facts Label